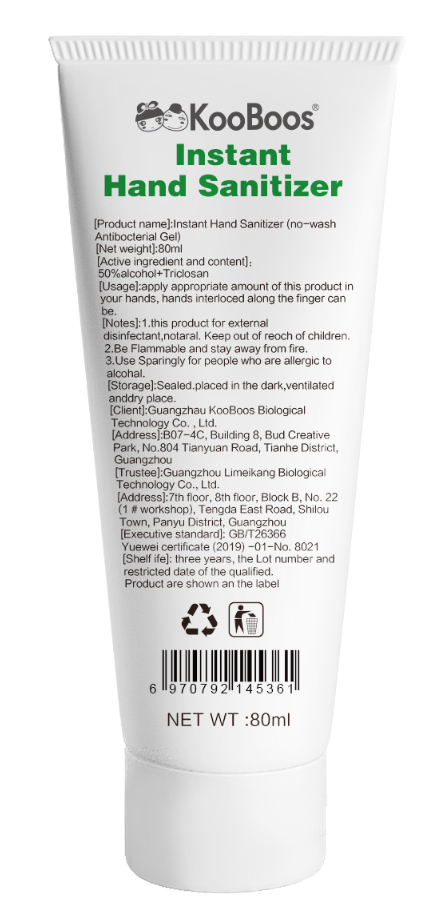 DRUG LABEL: KooBoos Instant Hand Sanitizer
NDC: 52966-005 | Form: LIQUID
Manufacturer: Guangzhou KooBoos Biological Technology Co., Ltd
Category: otc | Type: HUMAN OTC DRUG LABEL
Date: 20200420

ACTIVE INGREDIENTS: TRICLOSAN 0.176 mg/100 mL
INACTIVE INGREDIENTS: ALCOHOL; WATER; GLYCERIN; CARBOMER HOMOPOLYMER, UNSPECIFIED TYPE; TROLAMINE

WARNINGS

This product for external disinfectant,notaral. Keep out of reoch of children.
Be Flammable and stay away from fire.
Use Sparingly for people who are allergic to alcohal.

INDICATIONS AND USAGE

Apply appropriate amount of this product in your hands, hands interloced along the finger can be.

DOSAGE AND ADMINISTRATION

Sealed placed in the dark,ventilated anddry place.

PURPOSE

Disinfection
Sterilization
No Rinseing

INACTIVE INGREDIENT

Water ,ethanol,glycerin, carbomer ,triethanolamine.

ACTIVE INGREDIENT

Triclosan

keep out of reach of children